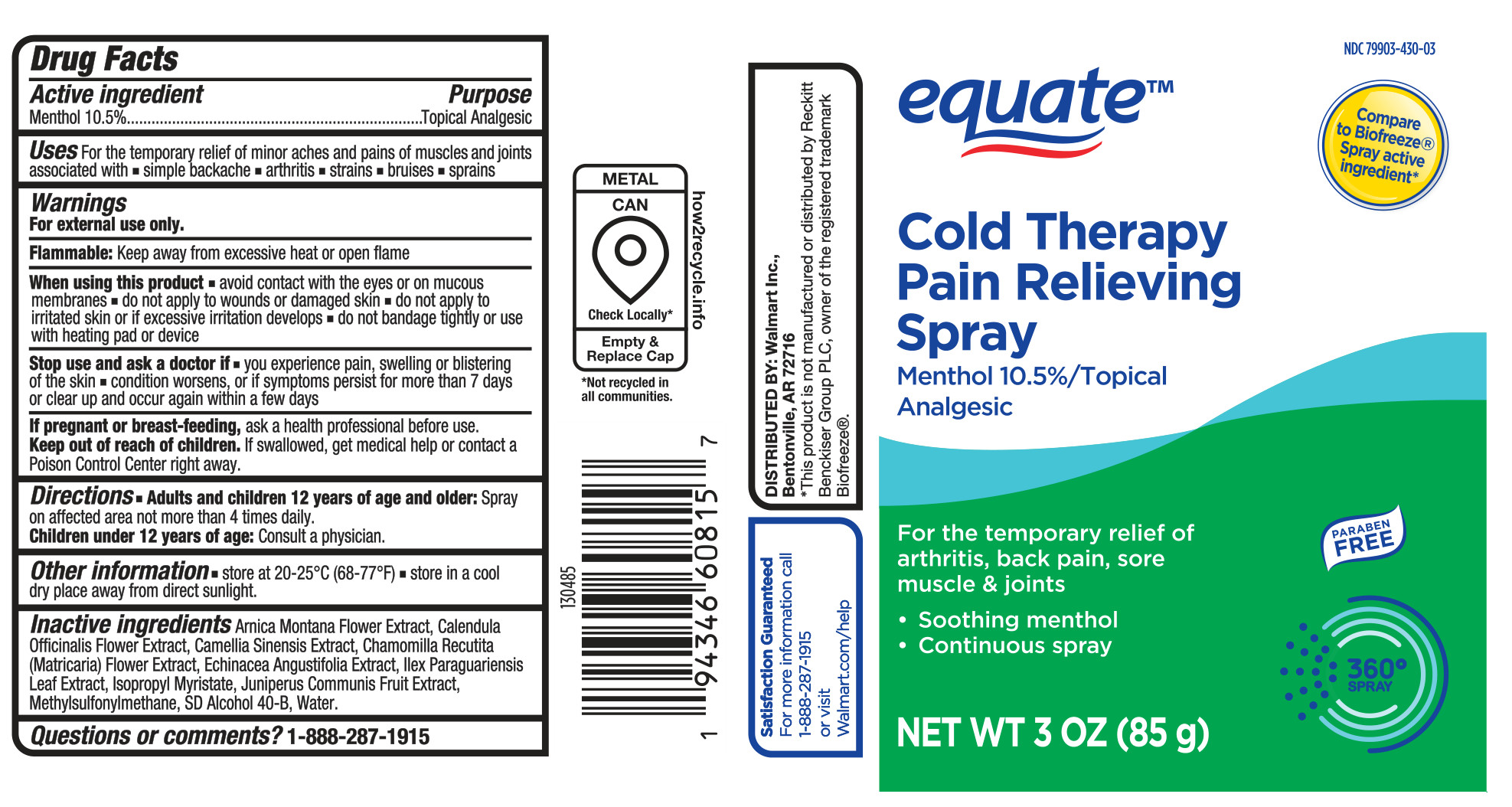 DRUG LABEL: Equate Cold Therapy Pain Relieving
NDC: 79903-430 | Form: SPRAY
Manufacturer: Walmart Inc
Category: otc | Type: HUMAN OTC DRUG LABEL
Date: 20260219

ACTIVE INGREDIENTS: MENTHOL, UNSPECIFIED FORM 105 mg/1 g
INACTIVE INGREDIENTS: ECHINACEA ANGUSTIFOLIA LEAF; GREEN TEA LEAF; ISOPROPYL MYRISTATE; CHAMOMILE; ALCOHOL; WATER; ARNICA MONTANA FLOWER WATER; ILEX PARAGUARIENSIS LEAF; DIMETHYL SULFONE; JUNIPER BERRY

Equate Cold Therapy Pain Relieving Spray

Active ingredient

Menthol 10.5%

Purpose

Topical Analgesic

Uses

For the temporary relief of minor aches and pains of muscles and joints associated with

- simple backache
- arthritis
- strains
- bruises
- sprains

Warnings

For external use only.

Flammable: Keep away from excessive heat or open flame

When using this product

- avoid contact with the eyes or on mucous membranes
- do no apply to wounds or damaged skin
- do not apply to irritated skin or if excessive irritation develops
- do not bandage tightly or use with heating pad or device

Stop use and ask a doctor if

- you experience pain, swelling or blistering of the skin
- condition worsens, or if symptoms persist for more than 7 days or clear up and occur again within a few days

If pregnant or breast-feeding,

ask a health professional before use.

Keep out of reach of children.

If swallowed, get medical help or contact a Poison Control Center right away.

Directions

- Adults and children 12 years of age and older: Spray on affected area not more than 4 times daily.
- Children under 12 years of age: Consult a physician.

Other information

- store at 20-25°C (68-77°F)
- store in a cool dry place away from direct sunlight

Inactive ingredients

Arnica Montana Flower Extract, Calendula Officinalis Flower Extract, Camellia Sinensis Extract, Chamomilla Recutita (Matricaria) Flower Extract, Echinacea Angustifolia Extract, Ilex Paraguariensis Leaf Extract, Isopropyl Myristate, Juniperus Communis Fruit Extract, Methylsulfonylmethane, SDS Alcohol 40-B, Water.

Questions or comments?

1-888-287-1915

Principal Dispal Panel - 85 g Can

equateTM

NDC 79903-430-03

Compare to Biofreeze® Spray active ingredient*

Cold Therapy

Pain Relieving

Spray

Menthol 10.5%/Topical

Analgesic

For the temporary relief of arthritis, back pain, sore muscle & joints

- Soothing menthol
- Continuous spray

Paraben Free

360° Spray

NET WT 3 OZ (85 g)